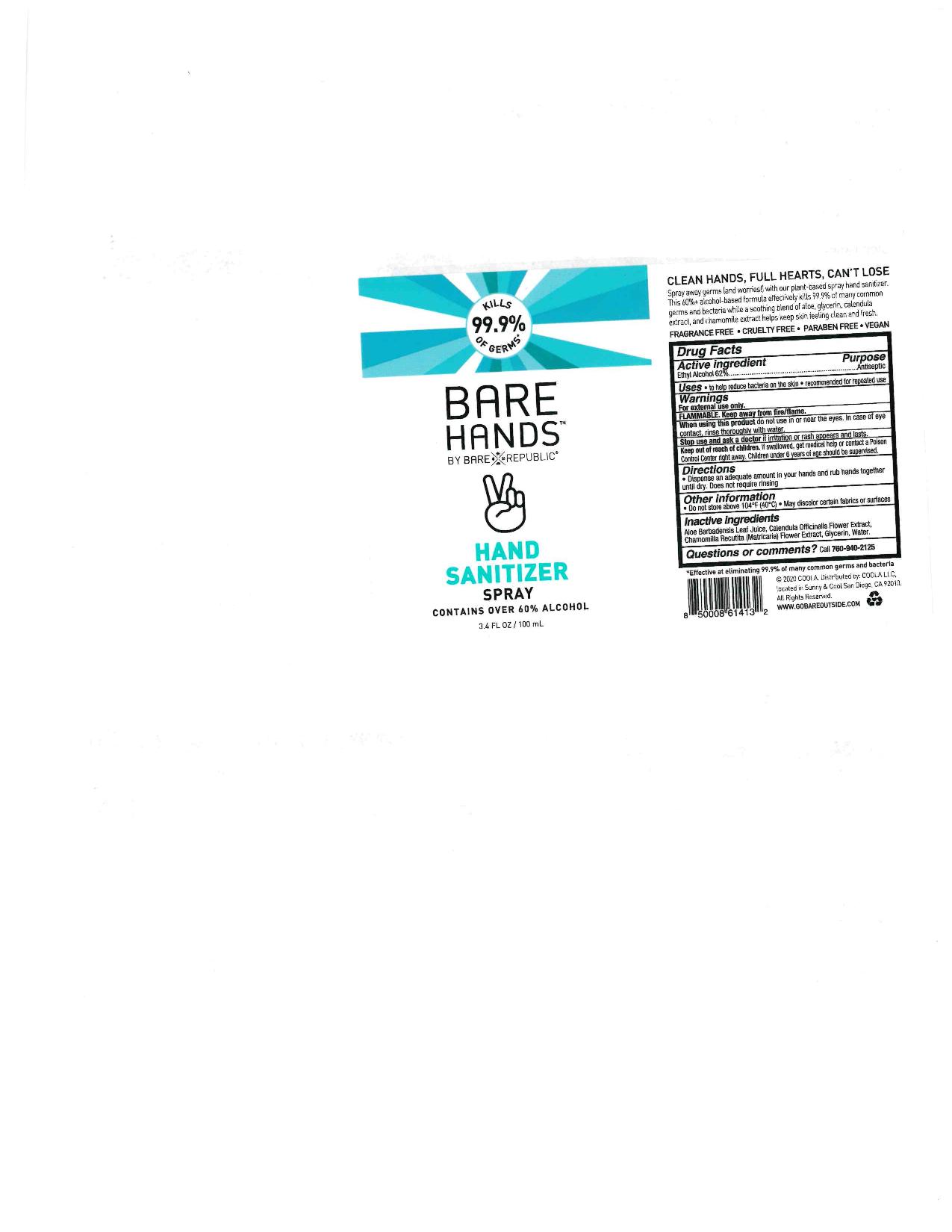 DRUG LABEL: Bare Hands
NDC: 76150-239 | Form: SPRAY
Manufacturer: Bell International Labroatories, Inc.
Category: otc | Type: HUMAN OTC DRUG LABEL
Date: 20200518

ACTIVE INGREDIENTS: ALCOHOL 62 mL/100 mL
INACTIVE INGREDIENTS: CHAMOMILE; WATER; ALOE VERA LEAF; GLYCERIN; CALENDULA OFFICINALIS FLOWER

Coola Bare Hands Hand Sanitizer Spray

Active Ingredient

Ethyl Alcohol 62%

Purpose

Antiseptic

Uses

to help reduce bacteria on the skin.

recommended for repeated use

RECENT MAJOR CHANGES

There was no changes. I was just reviewing the content.

Warnings

For external use only

Flammable. Keep away from fire/flame.

When using this product do not use in or near the eyes. In case of eye contact, rinse thoroughly with water.

Stop use and ask a dotor if irritaion or rash appears and lasts.

Keep out of reach of children. If swallowed, get medical help or contact a Poison Control Center right away. Children under 6 years of age should be supervised.

Directions

Dispense an adequate amount in your hands and rub hands together until dry. Does not require rinising.

Other information

Do not store above 104 F (40 C). May discolor certain fabrics or surfaces.

Inactive Ingredients

Aloe Barbadensis Leaf Juice, Calendula Officinalis Flower Extract, Chamomilla Recutita (Matricaria) Flower Extract, Glycerin, Water